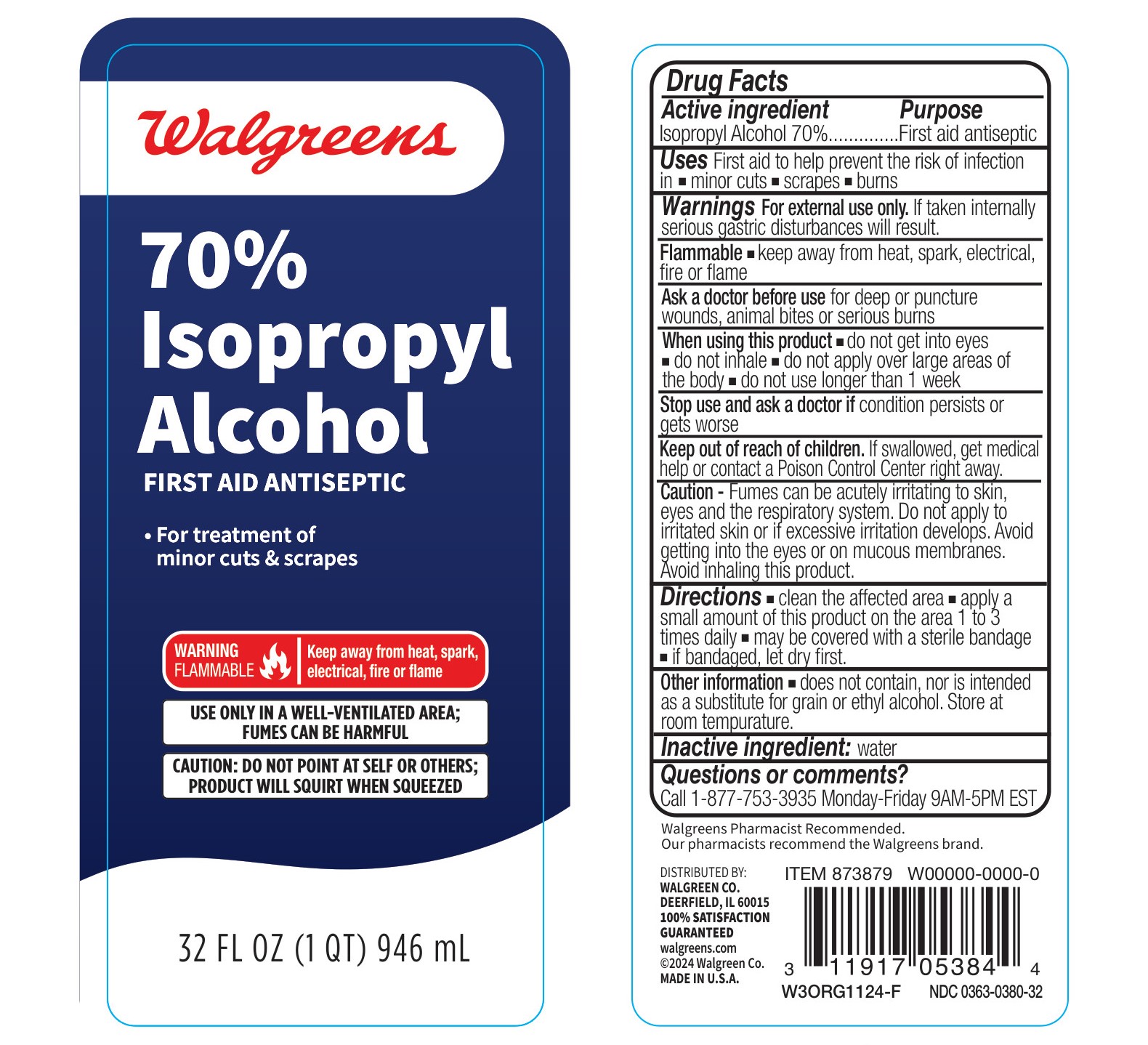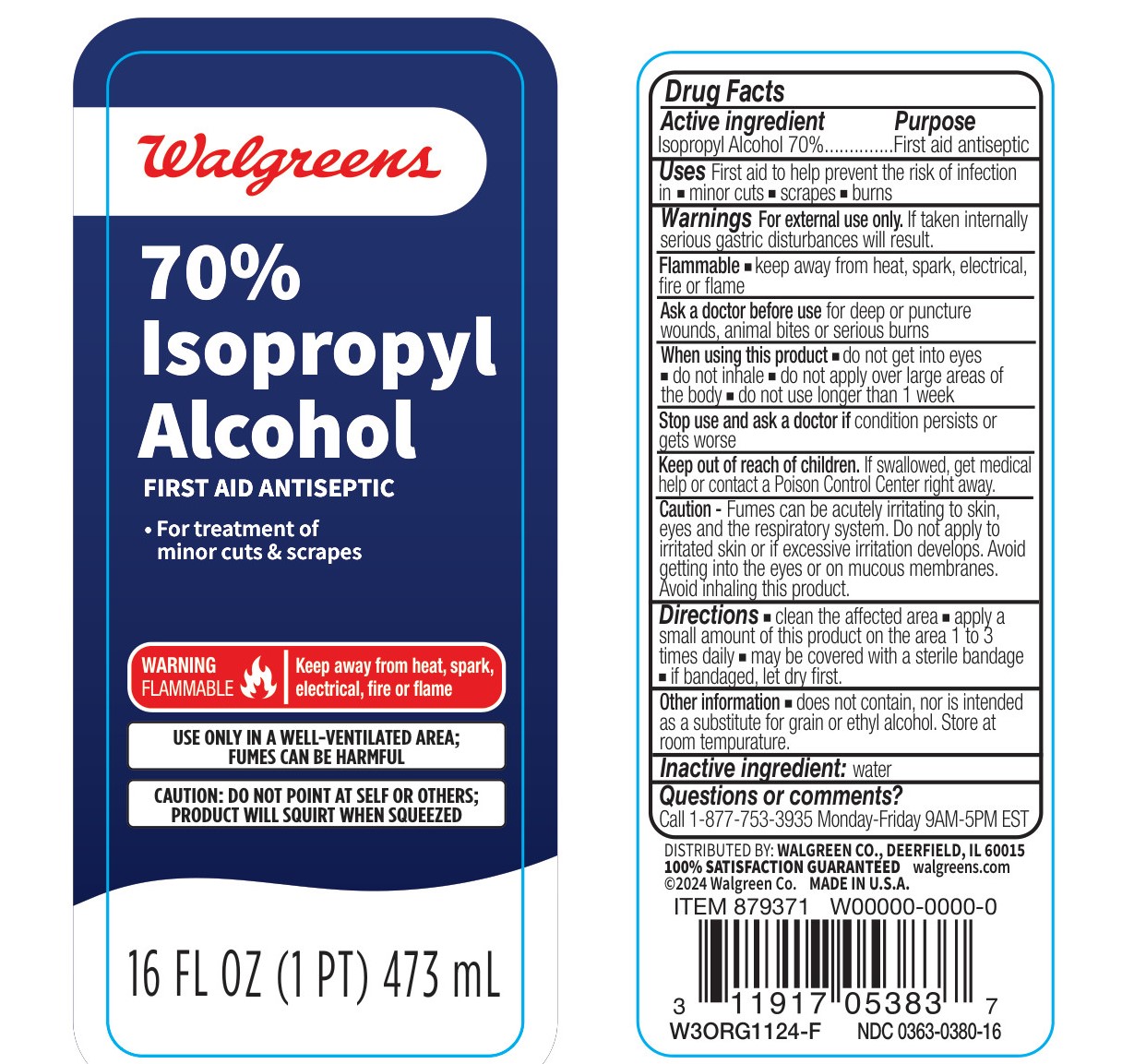 DRUG LABEL: Walgreens 70% Isopropyl Alcohol
NDC: 0363-0380 | Form: LIQUID
Manufacturer: Walgreen Co.
Category: otc | Type: HUMAN OTC DRUG LABEL
Date: 20241204

ACTIVE INGREDIENTS: ISOPROPYL ALCOHOL 0.7 mL/1 mL
INACTIVE INGREDIENTS: WATER

Walgreens 70% Isopropyl Alcohol

Active Ingredient

Isopropyl Alcohol 70%

Purpose

First aid antiseptic

Use

First aid to help prevent the risk of infection in

- minor cuts
- scrapes
- burns

Warnings

For external use only. If taken internally serious gastric disturbances will result.

Flammable: keep away from heat, spark, electrical, fire or flame.

Ask a doctor before use

for deep puncture wounds, animal bites or serious burns

When using this product

- do not get into eyes
- do not inhale
- do not apply over large areas of the body
- do not use longer than 1 week

Stop use and ask a doctor if

condition persists or gets worse

Keep out of reach of children

If swallowed, get medical help or contact a Poison Control Center right away.

Caution

Fumes can be acutely irritating to skin, eyes and the respiratory system. Do not apply to irritated skin or if excessive irritation develops. Avoid getting into the eyes or on mucous memebranes. Avoid inhaling this product.

Directions

- clean the affected area
- apply a small amount of this product on the area 1 to 3 times daily
- may be covered with a sterile bandage
- if bandaged, let dry first

Other information

- does not contain, nor is intended as a substitute for grain or ethyl alcohol.
- Store at room temperature.

Inactive ingredient

water

Questions or comments?

Call 1-877-753-3935 Monday-Friday 9AM-5PM EST

Pricipal Display Panel - 473 mL

Walgreens

70% Isopropyl Alcohol

FIRST AID ANTISEPTIC

- For treatment of minor cuts & scrapes

WARNING

FLAMMABLE

Keep away from heat, spark, electrical, fire or flame

USE ONLY IN A WELL-VENTILATED AREA; FUMES CAN BE HARMFUL

CAUTION: DO NOT POINT AT SELF OR OTHERS; PRODUCT WILL SQUIRT WHEN SQUEEZED

16 FL OZ (1 PT) 473 mL

Principal Display Panel - 946 mL

Walgreens

70% Isopropyl Alcohol

FIRST AID ANTISEPTIC

- For treatment of minor cuts & scrapes

WARNING

FLAMMABLE

Keep away from heat, spark, electrical, fire or flame

USE ONLY IN A WELL-VENTILATED AREA; FUMES CAN BE HARMFUL

CAUTION: DO NOT POINT AT SELF OR OTHERS; PRODUCT WILL SQUIRT WHEN SQUEEZED

32 FL OZ (1 QT) 946 mL